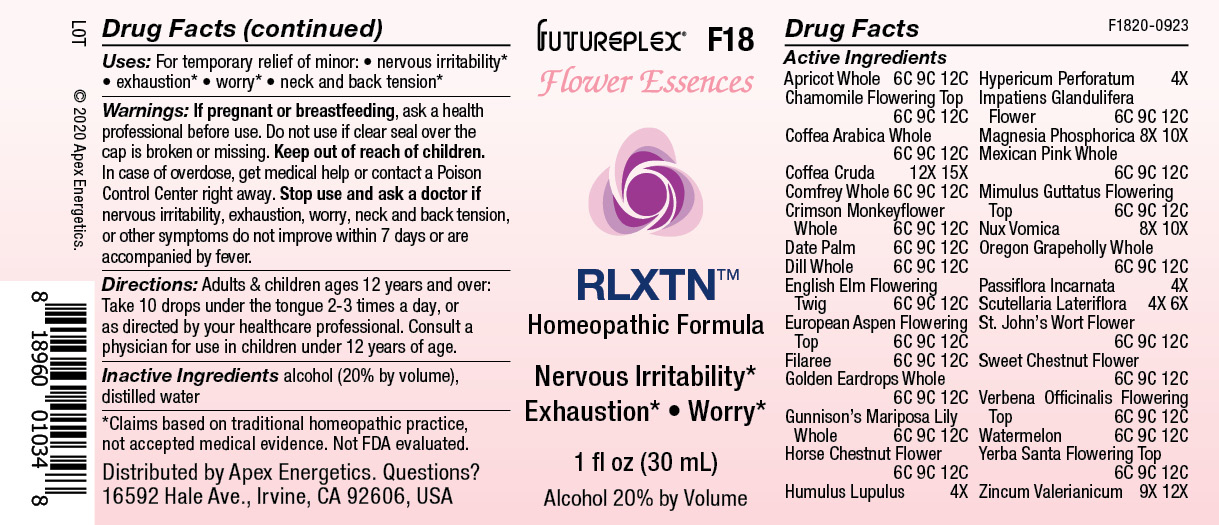 DRUG LABEL: F18
NDC: 63479-0618 | Form: SOLUTION/ DROPS
Manufacturer: Apex Energetics Inc.
Category: homeopathic | Type: HUMAN OTC DRUG LABEL
Date: 20240108

ACTIVE INGREDIENTS: ULMUS PROCERA FLOWERING TWIG 12 [hp_C]/1 mL; POPULUS TREMULA FLOWERING TOP 12 [hp_C]/1 mL; ERODIUM CICUTARIUM 12 [hp_C]/1 mL; CALOCHORTUS GUNNISONII WHOLE 12 [hp_C]/1 mL; HOPS 4 [hp_X]/1 mL; MAGNESIUM PHOSPHATE, DIBASIC TRIHYDRATE 10 [hp_X]/1 mL; MIMULUS GUTTATUS FLOWERING TOP 12 [hp_C]/1 mL; IMPATIENS GLANDULIFERA FLOWER 12 [hp_C]/1 mL; SILENE LACINIATA WHOLE 12 [hp_C]/1 mL; HYPERICUM PERFORATUM FLOWER 12 [hp_C]/1 mL; ANETHUM GRAVEOLENS WHOLE 12 [hp_C]/1 mL; AESCULUS HIPPOCASTANUM FLOWER 12 [hp_C]/1 mL; PRUNUS ARMENIACA WHOLE 12 [hp_C]/1 mL; ERYTHRANTHE CARDINALIS WHOLE 12 [hp_C]/1 mL; SYMPHYTUM OFFICINALE WHOLE 12 [hp_C]/1 mL; MATRICARIA RECUTITA FLOWERING TOP 12 [hp_C]/1 mL; COFFEA ARABICA WHOLE 12 [hp_C]/1 mL; ARABICA COFFEE BEAN 15 [hp_X]/1 mL; PHOENIX DACTYLIFERA WHOLE 12 [hp_C]/1 mL; EHRENDORFERIA CHRYSANTHA WHOLE 12 [hp_C]/1 mL; CASTANEA SATIVA FLOWER 12 [hp_C]/1 mL; HYPERICUM PERFORATUM 4 [hp_X]/1 mL; STRYCHNOS NUX-VOMICA SEED 10 [hp_X]/1 mL; BERBERIS AQUIFOLIUM WHOLE 12 [hp_C]/1 mL; PASSIFLORA INCARNATA FLOWERING TOP 4 [hp_X]/1 mL; VERBENA OFFICINALIS FLOWERING TOP 12 [hp_C]/1 mL; SCUTELLARIA LATERIFLORA WHOLE 6 [hp_X]/1 mL; WATERMELON 12 [hp_C]/1 mL; ERIODICTYON CALIFORNICUM FLOWERING TOP 12 [hp_C]/1 mL; ZINC VALERATE DIHYDRATE 12 [hp_X]/1 mL
INACTIVE INGREDIENTS: ALCOHOL; WATER

F18

Active Ingredients
Apricot Whole | 6C 9C 12C
Chamomile Flowering Top | 6C 9C 12C
Coffea Arabica Whole | 6C 9C 12C
Coffea Cruda | 12X 15X
Comfrey Whole | 6C 9C 12C
Crimson Monkeyflower Whole | 6C 9C 12C
Date Palm | 6C 9C 12C
Dill Whole | 6C 9C 12C
English Elm Flowering Twig | 6C 9C 12C
European Aspen Flowering Top | 6C 9C 12C
Filaree | 6C 9C 12C
Golden Eardrops Whole | 6C 9C 12C
Gunnison's Mariposa Lily Whole | 6C 9C 12C
Horse Chestnut Flower | 6C 9C 12C
Humulus Lupulus | 4X
Hypericum Perforatum | 4X
Impatiens Glandulifera Flower | 6C 9C 12C
Magnesia Phosphorica | 8X 10X
Mexican Pink Whole | 6C 9C 12C
Mimulus Guttatus Flowering Top | 6C 9C 12C
Nux Vomica | 8X 10X
Oregon Grapeholly Whole | 6C 9C 12C
Passiflora Incarnata | 4X
Scutellaria Lateriflora | 4X 6X
St. John's Wort Flower | 6C 9C 12C
Sweet Chestnut Flower | 6C 9C 12C
Verbena Officinalis Flowering Top | 6C 9C 12C
Watermelon | 6C 9C 12C
Yerba Santa Flowering Top | 6C 9C 12C
Zincum Valerianicum | 9X 12X

INDICATIONS AND USAGE

Uses:

For temporary relief of minor:

nervous irritability*

exhaustion*

worry*

neck and back tension*

*Claims based on traditional homeopathic practice, not accepted medical evidence. Not FDA evaluated.

Warnings:

PREGNANCY OR BREAST FEEDING

If pregnant or breastfeeding, ask a health professional before use.

Do not use if clear seal over the cap is broken or missing.

Keep out of reach of children. In case of overdose, get medical help or contact a Poison Control Center right away.

Stop use and ask a doctor if nervous irritability, exhaustion, worry, neck and back tension, or other symptoms do not improve within 7 days or are accompanied by fever.

Directions:

Adults & children ages 12 years and over: Take 10 drops under the tongue 2-3 times a day, or as directed by your healthcare professional. Consult a physician for use in children under 12 years of age.

Inactive Ingredients

alcohol (20% by volume), distilled water

Distributed by Apex Energetics. Questions?

16592 Hale Ave., Irvine, CA 92606, USA

PACKAGE LABEL

FUTUREPLEX® F18

Flower Essences

RLXTN™

Homeopathic Formula

Nervous Irritability*

Exhaustion*

Worry*

1 fl oz (30 mL)

Alcohol 20% by Volume